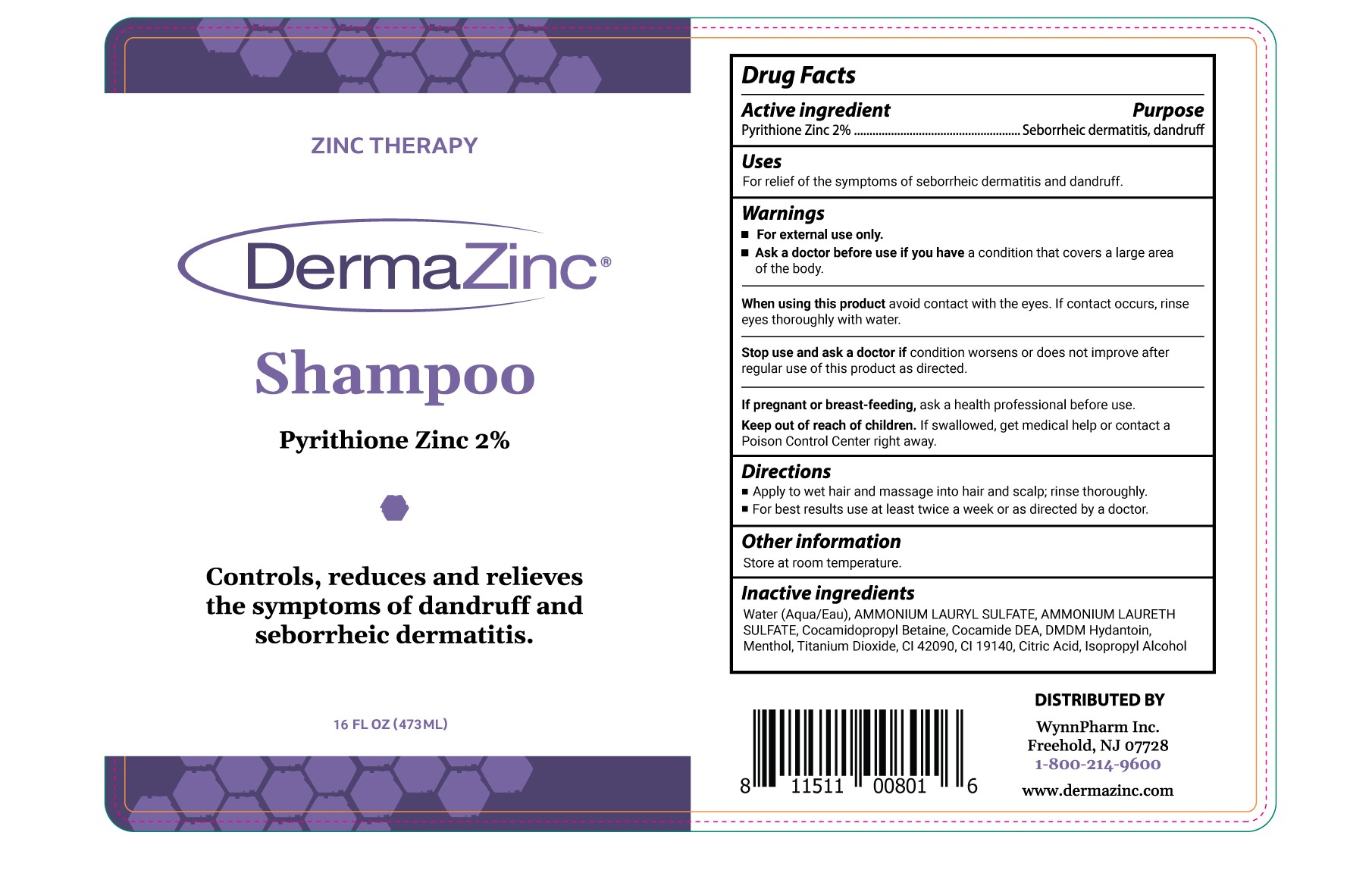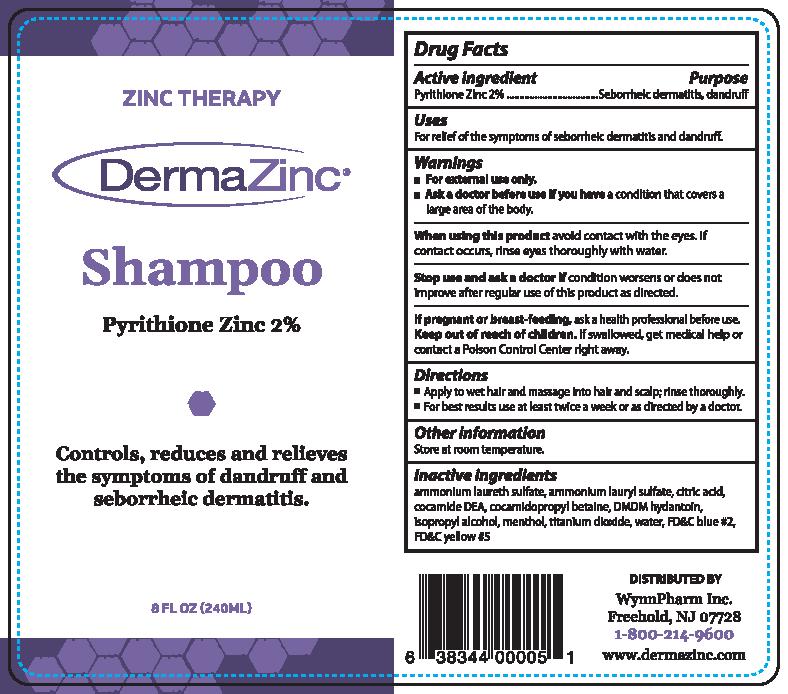 DRUG LABEL: DermaZinc
NDC: 35324-003 | Form: SHAMPOO
Manufacturer: WynnPharm Inc
Category: otc | Type: HUMAN OTC DRUG LABEL
Date: 20250525

ACTIVE INGREDIENTS: PYRITHIONE ZINC 2 g/100 mL
INACTIVE INGREDIENTS: ANHYDROUS CITRIC ACID; COCO DIETHANOLAMIDE; MENTHOL; TITANIUM DIOXIDE; FD&C BLUE NO. 2; AMMONIUM LAURETH-2 SULFATE; AMMONIUM LAURYL SULFATE; COCAMIDOPROPYL BETAINE; DMDM HYDANTOIN; ISOPROPYL ALCOHOL; WATER; FD&C YELLOW NO. 5

DermaZinc Shampoo

ACTIVE INGREDIENT

Pyrithione Zinc 2%

Keep Out of Reach of Children.

PURPOSE

Anti-dandruff

Seborrheic Dermatitis treatment

DOSAGE AND ADMINISTRATION

Apply to wet hair and massage into hair and scalp; rinse thoroughly

For best results use at least twice a week or as directed by a doctor.

INDICATIONS AND USAGE

For relief of the symptoms of seborrheic dermatitis and dandruff.

Warnings
■ For external use only.
■ Ask a doctor before use if you have a condition that covers a large area of the body.

When using this product avoid contact with the eyes. If contact occurs, rinse eyes thoroughly with
water.
Stop use and ask a doctor if condition worsens or does not improve after regular use of this
product as directed.

If pregnant or breast-feeding, ask a health professional before use. Keep out of reach of children.
If swallowed, get medical help or contact a Poison Control Center right away.

Inactive ingredients
ammonium laureth sulfate, ammonium lauryl sulfate, citric acid, cocamide DEA, cocamidopropyl
betaine, DMDM hydantoin, isopropyl alcohol, menthol, titanium dioxide, water, FD&C blue #2,
FD&C yellow #5